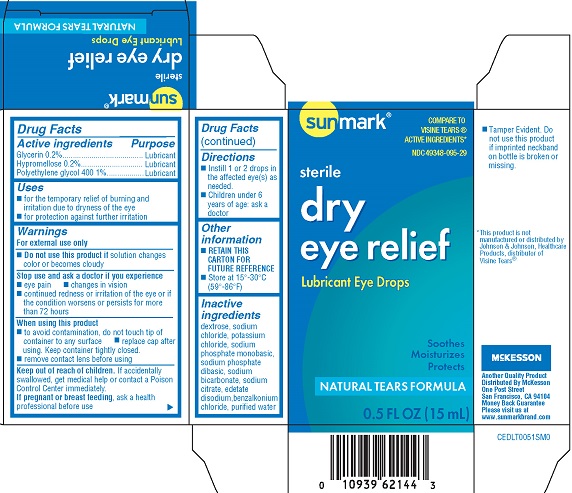 DRUG LABEL: Sunmark Dry Eye Relief
NDC: 49348-095 | Form: SOLUTION/ DROPS
Manufacturer: Strategic Sourcing Services LLC
Category: otc | Type: HUMAN OTC DRUG LABEL
Date: 20231223

ACTIVE INGREDIENTS: HYPROMELLOSES 0.2 g/100 mL; GLYCERIN 0.2 g/100 mL; POLYETHYLENE GLYCOL 400 1 g/100 mL
INACTIVE INGREDIENTS: DEXTROSE; SODIUM CHLORIDE; SODIUM PHOSPHATE, MONOBASIC; POTASSIUM CHLORIDE; SODIUM PHOSPHATE, DIBASIC; SODIUM BICARBONATE; SODIUM CITRATE; EDETATE DISODIUM; BENZALKONIUM CHLORIDE; WATER

Sunmark Dry Eye Relief (PLD)

Active ingredients

Glycerin 0.2%

Hypromellose 0.2%

Polyethylene glycol 1%

Purpose

Glycerin.....Lubricant

Hypromellose.....Lubricant

Polyethylene glycol 400.....Lubricant

Uses

- for the temporary relief of burning and irritation due to dryness of the eye
- for protection against further irritation

Warnings

For external use only

Do not use this product if solution changes color or becomes cloudy

Stop use and ask a doctor if you experience

- eye pain
- changes in vision
- continued redness or irritation of the eye or if the condition worsens or persists for more than 72 hours

When using this product

- to avoid contamination, do not touch tip of container to any surface
- replace cap after using. Keep container tightly closed
- remove contact lens before using

Keep out of reach of children

If accidentally swallowed get medical help or contact a Poison Control Center immediately

PREGNANCY OR BREAST FEEDING

If pregnant and breast-feeding, ask a health professional before use

Directions

- Instill 1 or 2 drops in the affected eye(s) as needed
- Children under 6 years of age: ask doctor

Other information

RETAIN THIS CARTON FOR FUTURE REFERENCE

Store at 15oC-30oC (59o-86oF)

Inactive ingredients

dextrose, sodium chloride, potassium chloride, sodium phosphate monobasic, sodium phosphate dibasic, sodium bicarbonate, sodium citrate, edetate disodium, benzalkonium chloride, purified water